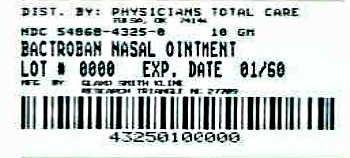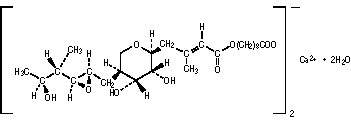 DRUG LABEL: BACTROBAN
NDC: 54868-4325 | Form: OINTMENT
Manufacturer: Physicians Total Care, Inc.
Category: prescription | Type: HUMAN PRESCRIPTION DRUG LABEL
Date: 20121024

ACTIVE INGREDIENTS: MUPIROCIN CALCIUM 20 mg/1 g
INACTIVE INGREDIENTS: PARAFFIN

BACTROBAN NASAL®
(mupirocin calcium ointment, 2%)
for intranasal use only

DESCRIPTION

BACTROBAN NASAL (mupirocin calcium ointment, 2%) contains the dihydrate crystalline calcium hemi-salt of the antibiotic mupirocin. Chemically, it is (αE,2S,3R,4R,5S)-5-[(2S,3S,4S,5S)-2,3-Epoxy-5-hydroxy-4-methylhexyl]tetrahydro-3,4-dihydroxy-β-methyl-2H-pyran-2-crotonic acid, ester with 9-hydroxynonanoic acid, calcium salt (2:1), dihydrate.

The molecular formula of mupirocin calcium is (C26H43O9)2Ca•2H2O, and the molecular weight is 1075.3. The molecular weight of mupirocin free acid is 500.6. The structural formula of mupirocin calcium is:

BACTROBAN NASAL is a white to off-white ointment that contains 2.15% w/w mupirocin calcium (equivalent to 2.0% pure mupirocin free acid) in a soft white ointment base. The inactive ingredients are paraffin and a mixture of glycerin esters (SOFTISAN® 649).

CLINICAL PHARMACOLOGY

Pharmacokinetics

Following single or repeated intranasal applications of 0.2 gram of BACTROBAN NASAL 3 times daily for 3 days to 5 healthy adult male subjects, no evidence of systemic absorption of mupirocin was demonstrated. The dosage regimen used in this study was for pharmacokinetic characterization only. (See DOSAGE AND ADMINISTRATION for proper clinical dosing information.)

In this study, the concentrations of mupirocin in urine and of monic acid in urine and serum were below the limit of determination of the assay for up to 72 hours after the applications. The lowest levels of determination of the assay used were 50 ng/mL of mupirocin in urine, 75 ng/mL of monic acid in urine, and 10 ng/mL of monic acid in serum. Based on the detectable limit of the urine assay for monic acid, one can extrapolate that a mean of 3.3% (range: 1.2 to 5.1%) of the applied dose could be systemically absorbed from the nasal mucosa of adults.

Data from a report of a pharmacokinetic study in neonates and premature infants indicate that, unlike in adults, significant systemic absorption occurred following intranasal administration of BACTROBAN NASAL in this population. At this time, the pharmacokinetic properties of mupirocin following intranasal application of BACTROBAN NASAL have not been adequately characterized in neonates or other children less than 12 years of age, and in addition, the safety of the product in children less than 12 years of age has not been established.

The effect of the concurrent application of intranasal mupirocin calcium ointment, 2% with other intranasal products has not been studied. (See PRECAUTIONS, Drug Interactions.)

Following intravenous or oral administration, mupirocin is rapidly metabolized. The principal metabolite, monic acid, demonstrates no antibacterial activity. In a study conducted in 7 healthy adult male subjects, the elimination half-life after intravenous administration of mupirocin was 20 to 40 minutes for mupirocin and 30 to 80 minutes for monic acid. Monic acid is predominantly eliminated by renal excretion. The pharmacokinetics of mupirocin has not been studied in individuals with renal insufficiency.

Microbiology

Mupirocin is an antibacterial agent produced by fermentation using the organism Pseudomonas fluorescens. Mupirocin inhibits bacterial protein synthesis by reversibly and specifically binding to bacterial isoleucyl transfer-RNA synthetase. Due to this mode of action, mupirocin demonstrates no in vitro cross-resistance with other classes of antimicrobial agents.

When mupirocin resistance does occur, it appears to result from the production of a modified isoleucyl-tRNA synthetase. High-level plasmid-mediated resistance (MIC >1,024 mcg/mL) has been reported in some strains of Staphylococcus aureus and coagulase-negative staphylococci.

Mupirocin is bactericidal at concentrations achieved topically by intranasal administration. However, the minimum bactericidal concentration (MBC) against relevant intranasal pathogens is generally 8-fold to 30-fold higher than the minimum inhibitory concentration (MIC). In addition, mupirocin is highly protein bound (>97%), and the effect of nasal secretions on the MICs of intranasally applied mupirocin has not been determined.

Mupirocin has been shown to be active against most strains of methicillin-resistant S. aureus, both in vitro and in clinical studies of the eradication of nasal colonization. BACTROBAN NASAL only has established clinical utility in nasal eradication as part of a comprehensive program to curtail institutional outbreaks of infections with methicillin-resistant S. aureus. (See INDICATIONS AND USAGE.)

The following in vitro data are available, but their clinical significance is unknown. Mupirocin exhibits in vitro MICs of 1 mcg/mL or less against most (>90%) strains of methicillin-susceptible S. aureus; however, the safety and effectiveness of mupirocin calcium in eradicating nasal colonization of and preventing subsequent infections due to methicillin-susceptible S. aureus have not been established.

INDICATIONS AND USAGE

BACTROBAN NASAL is indicated for the eradication of nasal colonization with methicillin-resistant S. aureus in adult patients and health care workers as part of a comprehensive infection control program to reduce the risk of infection among patients at high risk of methicillin-resistant S. aureus infection during institutional outbreaks of infections with this pathogen.

NOTE:

1. There are insufficient data at this time to establish that this product is safe and effective as part of an intervention program to prevent autoinfection of high-risk patients from their own nasal colonization with S. aureus.
2. There are insufficient data at this time to recommend use of BACTROBAN NASAL for general prophylaxis of any infection in any patient population.
3. Greater than 90% of subjects/patients in clinical trials had eradication of nasal colonization 2 to 4 days after therapy was completed. Approximately 30% recolonization was reported in 1 domestic study within 4 weeks after completion of therapy. These eradication rates were clinically and statistically superior to those reported in subjects/patients in the vehicle-treated arms of the adequate and well-controlled studies. Those treated with vehicle had eradication rates of 5% to 30% at 2 to 4 days post-therapy with 85% to 100% recolonization within 4 weeks.

All adequate and well-controlled trials of this product were vehicle-controlled; therefore, no data from direct, head-to-head comparisons with other products are available at this time.

CONTRAINDICATIONS

BACTROBAN NASAL is contraindicated in patients with known hypersensitivity to any of the constituents of the product.

WARNINGS

AVOID CONTACT WITH THE EYES. Application of BACTROBAN NASAL to the eye under testing conditions has caused severe symptoms such as burning and tearing. These symptoms resolved within days to weeks after discontinuation of the ointment.

In the event of a sensitization or severe local irritation from BACTROBAN NASAL, usage should be discontinued.

PRECAUTIONS

General

As with other antibacterial products, prolonged use may result in overgrowth of nonsusceptible microorganisms, including fungi. (See DOSAGE AND ADMINISTRATION.)

Information for Patients

Patients should be given the following instructions:

- Apply approximately one-half of the ointment from the single-use tube directly into 1 nostril and the other half into the other nostril;
- Avoid contact of the medication with the eyes;
- Discard the tube after using, do not re-use;
- Press the sides of the nose together and gently massage after application to spread the ointment throughout the inside of the nostrils; and
- Discontinue usage of the medication and call your healthcare practitioner if sensitization or severe local irritation occurs.

Drug Interactions

The effect of the concurrent application of intranasal mupirocin calcium and other intranasal products has not been studied. Until further information is known, mupirocin calcium ointment, 2% should not be applied concurrently with any other intranasal products.

Carcinogenesis, Mutagenesis, Impairment of Fertility

Long-term studies in animals to evaluate carcinogenic potential of mupirocin calcium have not been conducted.

Results of the following studies performed with mupirocin calcium or mupirocin sodium in vitro and in vivo did not indicate a potential for mutagenicity: Rat primary hepatocyte unscheduled DNA synthesis, sediment analysis for DNA strand breaks, Salmonella reversion test (Ames), Escherichia coli mutation assay, metaphase analysis of human lymphocytes, mouse lymphoma assay, and bone marrow micronuclei assay in mice.

Reproduction studies were performed in rats with mupirocin administered subcutaneously at doses up to 40 times the human intranasal dose (approximately 20 mg mupirocin per day) on a mg/m^2 basis and revealed no evidence of impaired fertility from mupirocin sodium.

Pregnancy

Teratogenic Effects: Pregnancy Category B

Reproduction studies have been performed in rats and rabbits with mupirocin administered subcutaneously at doses up to 65 and 130 times, respectively, the human intranasal dose (approximately 20 mg mupirocin per day) on a mg/m2 basis and revealed no evidence of harm to the fetus due to mupirocin. There are, however, no adequate and well-controlled studies in pregnant women. Because animal reproduction studies are not always predictive of human response, this drug should be used during pregnancy only if clearly needed.

Nursing Mothers

It is not known whether this drug is excreted in human milk. Because many drugs are excreted in human milk, caution should be exercised when BACTROBAN NASAL is administered to a nursing woman.

Pediatric Use

Safety in children under the age of 12 years has not been established. (See CLINICAL PHARMACOLOGY.)

ADVERSE REACTIONS

Clinical Trials

In clinical trials, 210 domestic and 2,130 foreign adult subjects/patients received BACTROBAN NASAL ointment. Less than 1% of domestic or foreign subjects and patients in clinical trials were withdrawn due to adverse events.

The most frequently reported adverse events in foreign clinical trials were as follows: Rhinitis (1.0%), taste perversion (0.8%), pharyngitis (0.5%).

In domestic clinical trials, 17% (36/210) of adults treated with BACTROBAN NASAL ointment reported adverse events thought to be at least possibly drug-related. The incidence of adverse events that were reported in at least 1% of adults enrolled in domestic clinical trials were as follows:

ADVERSE EVENTS (≥1% INCIDENCE)-ADULTS IN US TRIALS
 | % of Subjects/Patients Experiencing Event; BACTROBAN NASAL; (n=210)
Headache | 9%
Rhinitis | 6%
Respiratory disorder, including; upper respiratory tract congestion | 5%
Pharyngitis | 4%
Taste perversion | 3%
Burning/stinging | 2%
Cough | 2%
Pruritus | 1%

The following events thought possibly drug-related were reported in less than 1% of adults enrolled in domestic clinical trials: Blepharitis, diarrhea, dry mouth, ear pain, epistaxis, nausea, and rash.

All adequate and well-controlled clinical trials have been performed using BACTROBAN NASAL ointment, 2% in 1 arm and the vehicle ointment in the other arm of the study. No adequate and well-controlled safety data are available from direct, head-to-head comparative studies of this product and other products for this indication.

OVERDOSAGE

Following single or repeated intranasal applications of BACTROBAN NASAL to adults, no evidence for systemic absorption of mupirocin was obtained. Intravenous infusions of 252 mg, as well as single oral doses of 500 mg of mupirocin, have been well tolerated in healthy adult subjects. There is no information regarding local overdose of BACTROBAN NASAL or regarding oral ingestion of the nasal ointment formulation.

DOSAGE AND ADMINISTRATION

(See INDICATIONS AND USAGE.)

Adults (12 years of age and older): Approximately one-half of the ointment from the single-use tube should be applied into 1 nostril and the other half into the other nostril twice daily (morning and evening) for 5 days.

After application, the nostrils should be closed by pressing together and releasing the sides of the nose repetitively for approximately 1 minute. This will spread the ointment throughout the nares.

The single-use 1.0 gram tube will deliver a total of approximately 0.5 grams of the ointment (approximately 0.25 grams/nostril).

The tube should be discarded after usage; it should not be re-used.

The safety and effectiveness of applications of this medication for greater than 5 days have not been established. There are no human clinical or pre-clinical animal data to support the use of this product in a chronic manner or in manners other than those described in this package insert.

Until further information is known, BACTROBAN NASAL should not be applied concurrently with any other intranasal products.

HOW SUPPLIED

BACTROBAN NASAL is supplied in 1.0-gram tubes.

NDC 54868-4325-0 (package of 10 single-tube cartons).

Store between 20° and 25°C (68° and 77°F); excursions permitted to 15°-30°C (59°-86°F). Do not refrigerate.

REFERENCE

1. Clinical and Laboratory Standards Institute (CLSI). Methods for Dilution Antimicrobial Susceptibility Tests for Bacteria That Grow Aerobically. Approved Standard. CLSI Document M7-A7. CLSI, Wayne, PA, January 2006.

BACTROBAN NASAL is a registered trademark of GlaxoSmithKline.

SOFTISAN is a registered trademark of Sasol Olefins & Surfactants GmbH.

GlaxoSmithKline

Research Triangle Park, NC 27709

©2009, GlaxoSmithKline. All rights reserved.

April 2009 BBN:2PI

Additional barcode labeling by:
Physicians Total Care, Inc.
Tulsa, Oklahoma 74146

PACKAGE LABEL

Principal Display Panel

NDC 54868-4325-0

BACTROBAN NASAL®

MUPIROCIN CALCIUM OINTMENT 2%

1 x 1.0 gram Single-Use Tube

Rx only

Store at 20o - 25oC (68o – 77oF); excursions permitted 15o - 30oC (59o – 86oF).. Do not refrigerate. Each gram contains 21.5 mg mupirocin calcium in a soft white ointment base.

Usual Dosage: For intranasal use only. Apply one-half the contents of a tube in one nostril. Apply other half of tube contents in other nostril. See accompanying prescribing information.

TO OPEN

1. Turn cap counter-clockwise to puncture the seal.

2. Lift off plastic tip cover.

HOW TO APPLY

Apply one-half the contents of the tube in one nostril.

Apply the other half of tube contents in the other nostril.

Press nostrils together. Massage for approximately one minute. Discard tube. Do not reuse.

Avoid contact with eyes. Contact your healthcare professional if you have any questions.

10000000067584